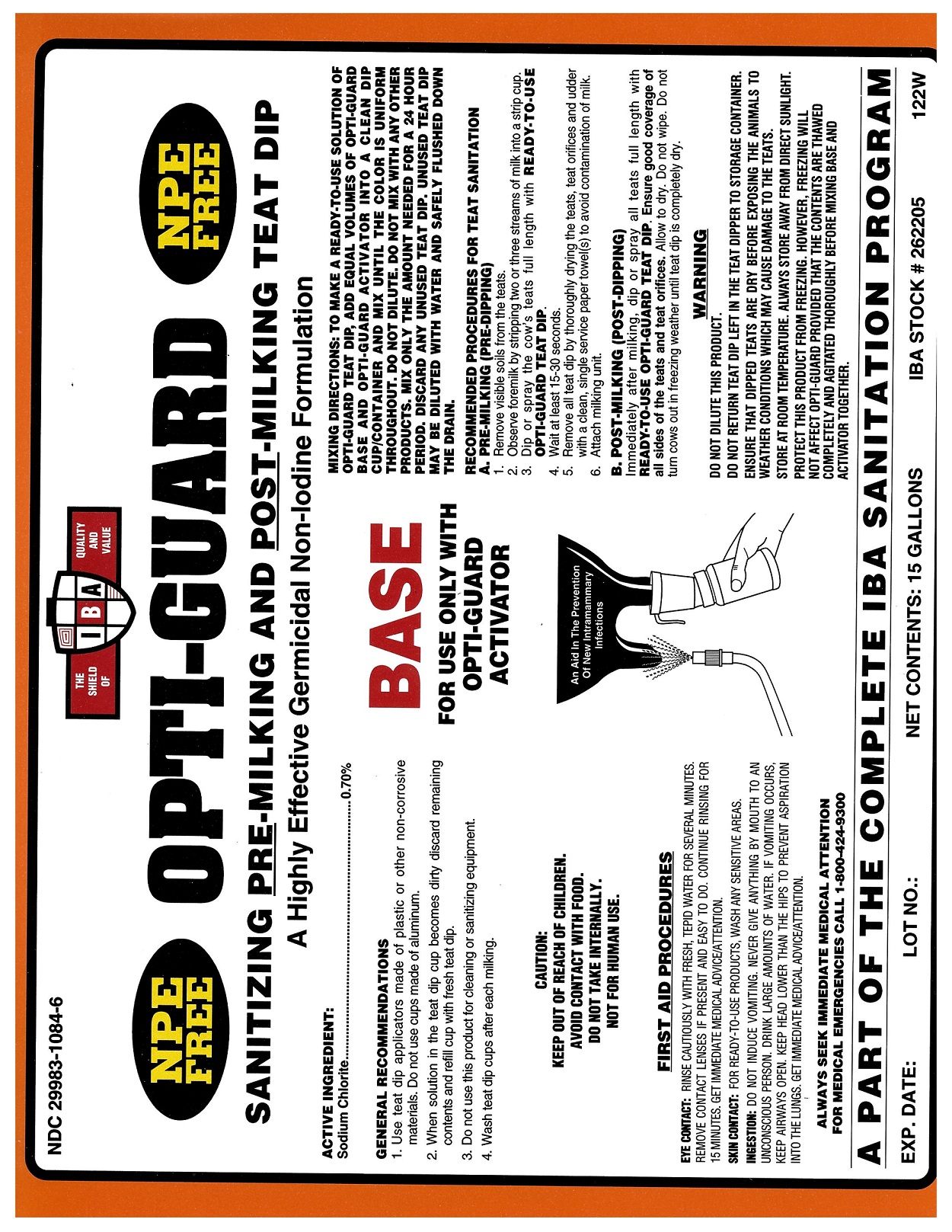 DRUG LABEL: Opti-Guard Base
NDC: 29983-1084 | Form: LIQUID
Manufacturer: IBA
Category: animal | Type: OTC ANIMAL DRUG LABEL
Date: 20251209

ACTIVE INGREDIENTS: SODIUM CHLORITE 0.7 kg/100 kg

Opti-Guard Base

Active Ingredient

Sodium Chlorite 0.7%

MIXING DIRECTIONS

TO MAKE A READY-TO-USE SOLUTION OF OPTI-GUARD TEAT DIP, ADD EQUAL VOLUMES OF OPTI-GUARD BASE AND OPTI-GUARD ACTIVATOR INTO A CLEAN DIP CUP/CONTAINER AND MIX UNTIL THE COLOR IS UNIFORM THROUGHOUT. DO NOT DILUTE. DO NOT MIX WITH ANY OTHER PRODUCTS. MIX ONLY THE AMOUNT NEEDED FOR A 24 HOUR PERIOD. DISCARD ANY UNUSED TEAT DIP. UNUSED TEAT DIP MAY BE DILUTED WITH WATER AND SAFELY FLUSHED DOWN THE DRAIN.

Recommended Procedures for Teat Sanitation

A. PRE-MILKING (PRE-DIPPING)

1. Remove visible soils from the teats.

2. Observe foremilk by stripping two or three streams of milk into a strip cup.

3. Dip or spray the cow's teats full lenght with READY-TO-USE OPTI-GUARD TEAT DIP.

4. Wait at least 15-30 seconds.

5. Remove all teat dip by thoroughly drying the teats, teat orifices and udder with a clean, single service paper towel(s) to avoid contamination of milk.

6. Attach milking unit.

B. POST-MILKING (POST-DIPPING)

Immediately after milking, dip or spray all teats full length with READY-TO-USE OPTI-GUARD TEAT DIP. Ensure good coverage of all sides of the teats and teat orifices. Allow to dry. Do not wipe. Do not turn cows out in freezing weather until teat dip is completely dry.

CAUTION

KEEP OUT OF REACH OF CHILDREN.

AVOID CONTACT WITH FOOD.

DO NOT TAKE INTERNALLY.

NOT FOR HUMAN USE.

FIRST AID PROCEDURES

EYE CONTACT: Rinse cautiously with fresh, tepid water for several minutes. Remove contact lenses if present and easy to do. Continue rinsing for 15 minutes. Get immediate medical advice/attention. SKIN CONTACT: For RTU products wash any sensitive areas. INGESTION: Do not induce vomitting. Never give anything by mouth to an unconscious person. Drink large amounts of water. If vomitting occurs, keep airways open. Keep head lower than the hips to prevent aspiration into the lungs. Get immediate medical advice/attention.

WARNING

DO NOT DILUTE THIS PRODUCT.

DO NOT RETURN TEAT DIP LEFT IN THE TEAT DIPPER TO STORAGE CONTAINER.

ENSURE THAT DIPPED TEATS ARE DRY BEFORE EXPOSING THE ANIMALS TO WEATHER CONDITIONS WHICH MAY CAUSE DAMAGE TO TO THE TEATS.

STORE AT ROOM TEMPERATURE. ALWAYS STORE AWAY FROM DIRECT SUNLIGHT.

PROTECT THIS PRODUCT FROM FREEZING. HOWEVER, FREEZING WILL NOT AFFECT OPTI-GUARD PROVIDED THAT THE CONTENTS ARE THAWED COMPLETELY AND AGITATED THOROUGLY BEFORE MIXING BASE AND ACTIVATOR TOGETHER.